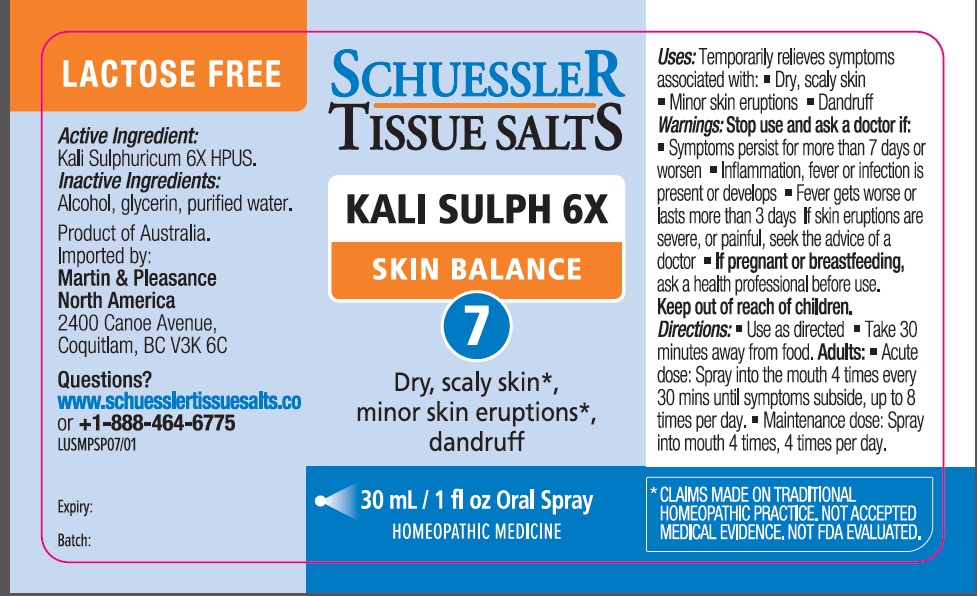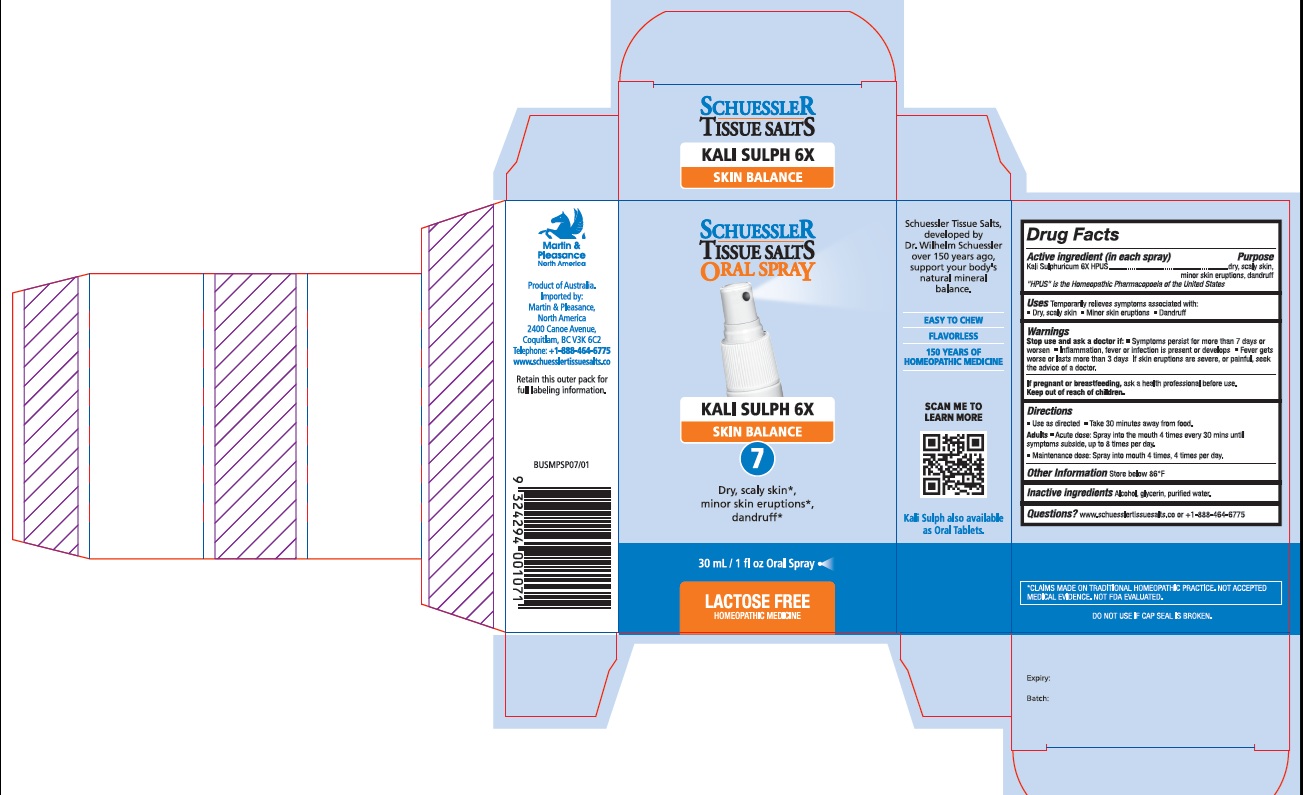 DRUG LABEL: Schuessler Tissue Salts Kali Sulph Skin Balance 7
NDC: 84999-007 | Form: SPRAY
Manufacturer: Martin & Pleasance Pty Ltd
Category: homeopathic | Type: HUMAN OTC DRUG LABEL
Date: 20250707

ACTIVE INGREDIENTS: POTASSIUM SULFATE 6 [hp_X]/30 mL
INACTIVE INGREDIENTS: ALCOHOL; GLYCERIN; WATER

Active Ingredients Purpose

Kali Sulphuricum 6X dry, scaly skin, minor skin eruptions,dandruff

“ HPUS” is the Homeopathic Pharmacopoeia of the United States

Uses

Temporarily relieves symptoms associated with:

- Dry, scaly skin
- Minor skin eruptions
- Dandruff

Warnings

Stop use and ask a doctor if

• Symptoms persist for more than 7 days or worsen

• Inflammation, fever or infection is present or develops

• Fever gets worse or lasts more than 3 days If skin eruptions are severe, or painful, seek the advice of a doctor.

If pregnant or breastfeeding, ask a health professional before use. Keep out of reach of children.

Directions

- Use as directed
- Take 30 minutes away from food.

Adults

- Acute dose: Spray into the mouth 4 times every 30 mins until symptoms subside, up to 8 times per day.
- Maintenance dose: Spray into mouth 4 times, 4 times per day.

Other lnformation

Store below 86°F

Inactive Ingredients

Alcohol, Glycerin, Purified Water

Questions?www.schuesslertissuesalts.co or + 1-888-464-6775